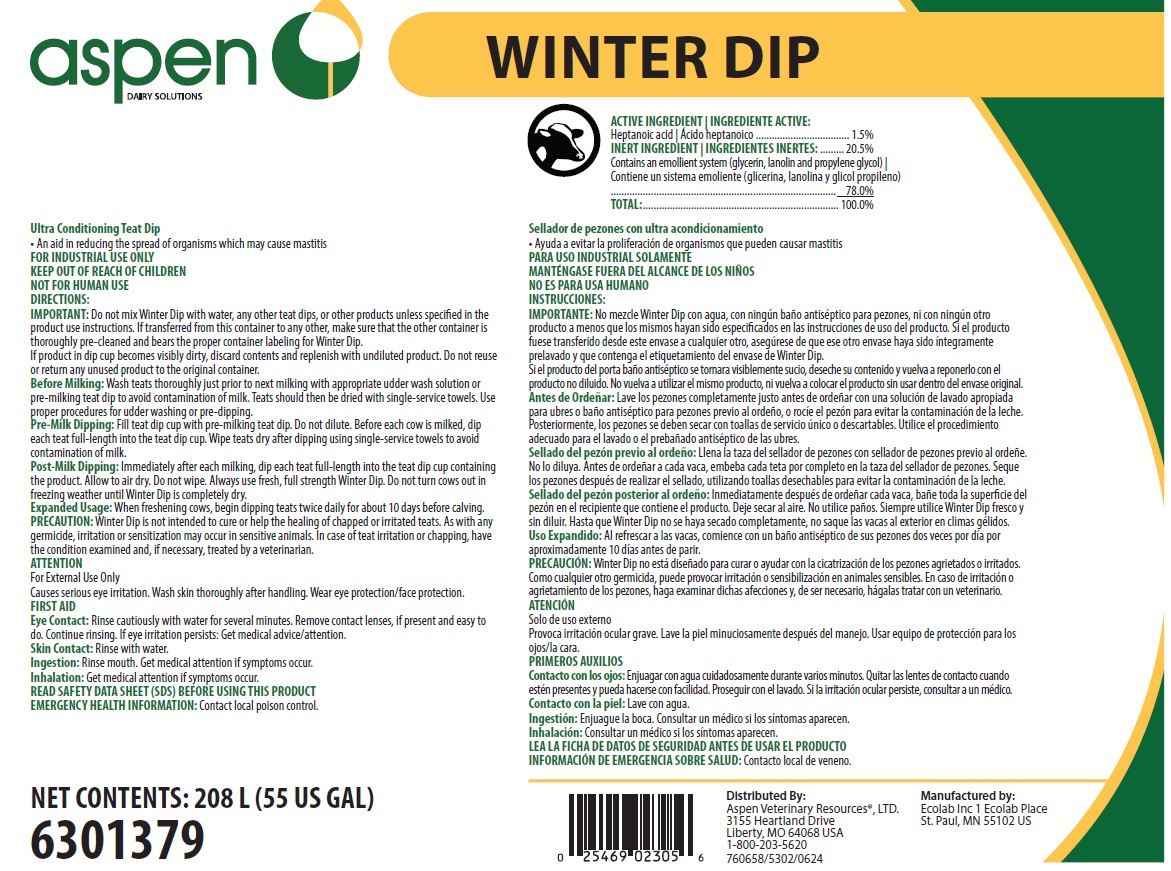 DRUG LABEL: Winter Dip
NDC: 46066-405 | Form: SOLUTION
Manufacturer: spen Veterinary Resources, Ltd.
Category: animal | Type: OTC ANIMAL DRUG LABEL
Date: 20250626

ACTIVE INGREDIENTS: HEPTANOIC ACID 15 mg/1 mL
INACTIVE INGREDIENTS: WATER; PROPYLENE GLYCOL; GLYCERIN; PEG-75 LANOLIN

SAFE HANDLING WARNING

FOR INDUSTRIAL USE ONLY

KEEP OUT OF REACH OF CHILDREN

NOT FOR HUMAN USE

ATTENTION

For External Use Only

Causes serious eye irritation. Wash skin thoroughly after handling. Wear eye protection/face protection.

DIRECTIONS:

IMPORTANT: Do not mix Winter Dip with water, any other teat dips, or other products unless specified in the product use instructions. If transferred from this container to any other, make sure that the other container is thoroughly pre-cleaned and bears the proper container labeling for Winter Dip.

If product in dip cup becomes visibly dirty, discard contents and replenish with undiluted product. Do not reuse or return any unused product to the original container.

Before Milking: Wash teats thoroughly just prior to next milking with appropriate udder wash solution or pre-milking teat dip to avoid contamination of milk. Teats should then be dried with single-service towels. Use proper procedures for udder washing or pre-dipping.

Pre-Milk Dipping: Fill teat dip cup with pre-milking teat dip. Do not dilute. Before each cow is milked, dip each teat full-length into the teat dip cup. Wipe teats dry after dipping using single-service towels to avoid contamination of milk.

Post-Milk Dipping: Immediately after each milking, dip each teat full-length into the teat dip cup containing the product. Allow to air dry. Do not wipe. Always use fresh, full strength Winter Dip. Do not turn cows out in freezing weather until Winter Dip is completely dry.

Expanded Usage: When freshening cows, begin dipping teats twice daily for about 10 days before calving.

PRECAUTION: Winter Dip is not intended to cure or help the healing of chapped or irritated teats. As with any germicide, irritation or sensitization may occur in sensitive animals. In case of teat irritation or chapping, have the condition examined and, if necessary, treated by a veterinarian.

OTHER SAFETY INFORMATION

FIRST AID

Eye Contact: Rinse cautiously with water for several minutes. Remove contact lenses, if present and easy to do. Continue rinsing. If eye irritation persists: Get medical advice/attention.

Skin Contact: Rinse with water.

Ingestion: Rinse mouth. Get medical attention if symptoms occur.

Inhalation: Get medical attention if symptoms occur.

READ SAFETY DATA SHEET (SDS) BEFORE USING THIS PRODUCT

EMERGENCY HEALTH INFORMATION: Contact local poison control.

Representative label and principal display panel

aspen DAIRY SOLUTIONS

WINTER DIP

Ultra Conditioning Teat Dip

- An aid in reducing the spread of organisms which may cause mastitis

ACTIVE INGREDIENT:

Heptanoic acid.................................................................. 1.5%

INERT INGREDIENTS:................................................... 20.5%

Contains an emollient system (glycerin, lanolin and propylene glycol)....78.0%

TOTAL:.......................................................................... 100.0%

NET CONTENTS: 208L (55 US GAL)

6301379

Distributed By:

Aspen Veterinary Resources®, Ltd.

3155 Heartland Drive, Liberty, MO 64068

1-800-203-5620

Manufactured by:

Ecolab Inc 1 Ecolab Place

St. Paul, MN 55102 US